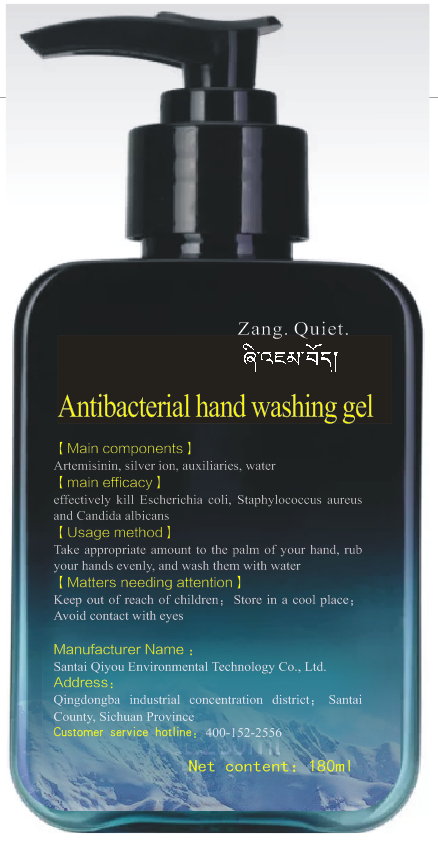 DRUG LABEL: Antibacterial hand washing gel
NDC: 40953-001 | Form: GEL
Manufacturer: Santai Qiyou Environmental Technology Co., Ltd.
Category: otc | Type: HUMAN OTC DRUG LABEL
Date: 20200508

ACTIVE INGREDIENTS: SILVER CATION 1.98 g/180 mL; ALCOHOL 0.36 mL/180 mL
INACTIVE INGREDIENTS: CARBOMER HOMOPOLYMER, UNSPECIFIED TYPE; WATER; ARTEMISININ; TROLAMINE

DOSAGE AND ADMINISTRATION

Store in a cool place

INACTIVE INGREDIENT

Artemisinin

Carbomer

triethanolamine

deionized water

INDICATIONS AND USAGE

Take appropriate amount to the palm of your hand, rub your hands evenly, and wash them with water

ACTIVE INGREDIENT

silver ion

Absolute ethanol

keep out of reach of children

PURPOSE

Disinfection
Sterilization

Keep out of reach of children; Store in a cool place;Avoid contact with eyes